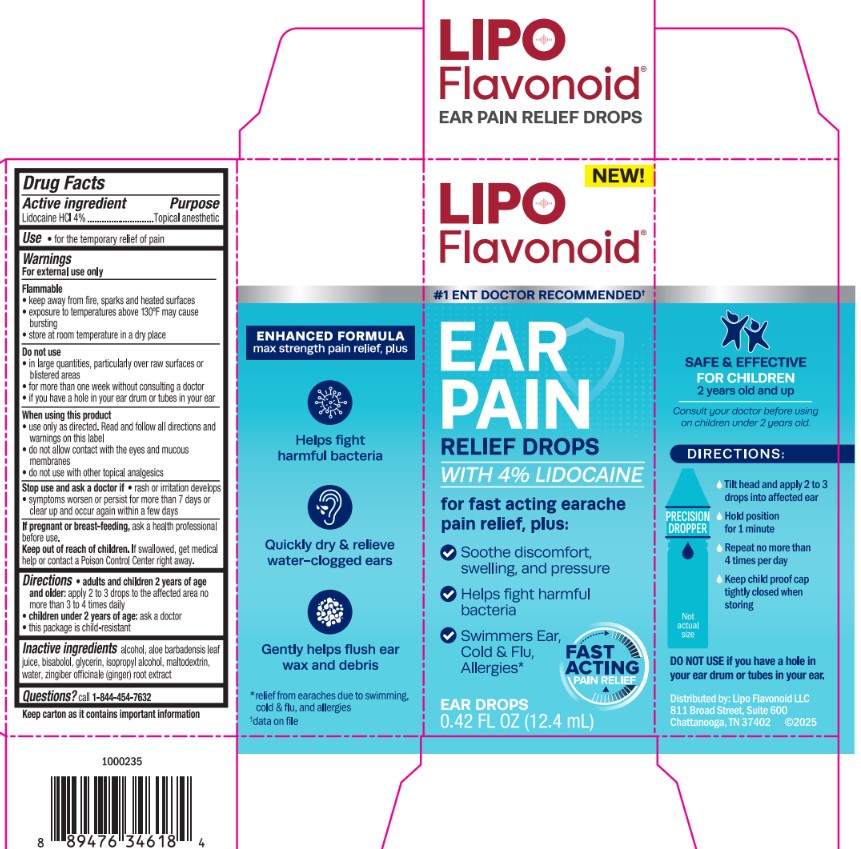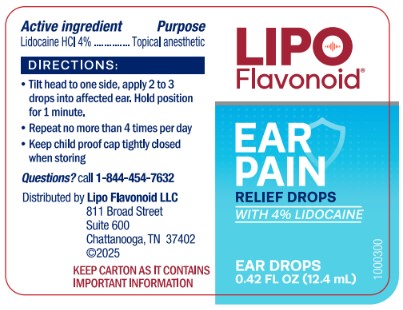 DRUG LABEL: Lipo Flavonoid Ear Pain Relief Drops with 4% Lidocaine
NDC: 69693-901 | Form: LIQUID
Manufacturer: Clarion Brands LLC
Category: otc | Type: HUMAN OTC DRUG LABEL
Date: 20250206

ACTIVE INGREDIENTS: LIDOCAINE HYDROCHLORIDE 4 g/100 mL
INACTIVE INGREDIENTS: BISABOLOL; ZINGIBER OFFICINALE (GINGER) ROOT OIL; WATER; MALTODEXTRIN; GLYCERIN; ALCOHOL; ISOPROPYL ALCOHOL; ALOE BARBADENSIS LEAF

ACTIVE INGREDIENT

Lidocaine HCl 4%

PURPOSE

Topical anesthetic

INDICATIONS AND USAGE

- for the temporary relief of pain

WARNINGS

For external use only

Flammable

- keep away from fire, sparks, and heated surfaces
- exposure to temperatures above 130°F may cause bursting
- store at room temperature in a dry place

Do not use

- in large quantities, particularly over raw surfaces or blistered areas
- for more than one week without consulting a doctor
- if you have a hole in your ear drum or tubes in your ear

WHEN USING

- use only as directed. Read and follow all directions and warning on this label
- do not allow contact with the eyes and mucous membranes
- do not use with other topical analgesics

Directions

- adults and children 2 years of age and older: apply to the affected area no more than 3 to 4 times daily
- children under 2 years of age: ask a doctor
- this package is child-resistant

INACTIVE INGREDIENT

alcohol

aloe barbadensis leaf juice

bisabolol, glycerin

isopropyl alcohol

maltodextrin

water

zingiber officinale (ginger) root extract

QUESTIONS

call 1-844-454-7632

DOSAGE AND ADMINISTRATION

Lidocaine HCl 4%

Topical anesthetic

Stop use and ask a doctor if

■ rash or irritation develops

■ if symptoms worsen or persist for more than 7 days or clear up and occur again within a few days

KEEP OUT OF REACH OF CHILDREN

If swallowed, get medical help or contact a Poison Control Center right away.

PACKAGE LABEL

NEW!

LipoFlavonoid®

#1 ENT DOCTOR RECOMMENDED†

EAR PAIN RELIEF DROPS WITH 4% LIDOCAINE

for fast acting earache pain relief, plus:

- Soothe discomfort, swelling, and pressure
- Helps fight harmful bacteria
- Swimmers Ear, Cold & Flu, Allergies*

FAST ACTING PAIN RELIEF

EAR DROPS 0.42 FL OZ (12.4 mL)

SAFE & EFFECTIVE FOR CHILDREN 2 years old and up

Consult your doctor before using on children under 2 years old.

DIRECTIONS:

- Tilt head and apply 2 to 3 drops into affected ear
- Hold position for 1 minute
- Repeat no more than 4 times per day
- Keep child proof cap tightly closed when stroring

DO NOT USE if you have a hole in your ear drum or tubes in your ear.

Distributed by: Lipo Flavonoid LLC

811 Broad Street, Suite 600

Chattanooga, TN 37402 ©2025

ENHANCED FORMULA max strength pain relief, plus

Helps fight harmful bacteria

Quickly dry & relieve water-clogged ears

Gently helps flush ear wax and debris

*relief from earaches due to swimming, cold & flu, and allergies

†data on file